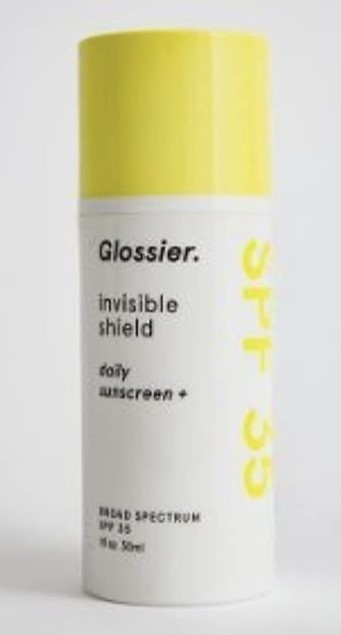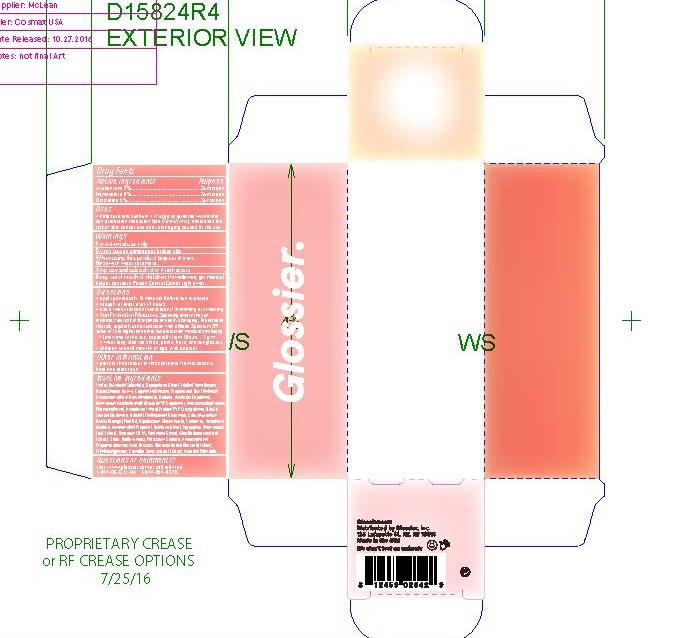 DRUG LABEL: GLOSSIER INVISIBLE SHIELD DAILY SUNSCREEN BROAD SPECTRUM SPF 35
NDC: 68577-152 | Form: LOTION
Manufacturer: COSMAX USA, CORPORATION
Category: otc | Type: HUMAN OTC DRUG LABEL
Date: 20241226

ACTIVE INGREDIENTS: AVOBENZONE 3 mg/100 mg; HOMOSALATE 6 mg/100 mg; OCTISALATE 5 mg/100 mg
INACTIVE INGREDIENTS: PENTYLENE GLYCOL; HYDROXYPHENYL PROPAMIDOBENZOIC ACID; WATER; BUTYLOCTYL SALICYLATE; DIPROPYLENE GLYCOL; METHYL TRIMETHICONE; BIOSACCHARIDE GUM-4; CAPRYLYL TRIMETHICONE; PROPANEDIOL; BIS-ETHYLHEXYL HYDROXYDIMETHOXY BENZYLMALONATE; BETAINE; AMMONIUM ACRYLOYLDIMETHYLTAURATE/VP COPOLYMER; PHENOXYETHANOL; HYDROLYZED WHEAT PROTEIN (ENZYMATIC, 3000 MW); DIBUTYL LAUROYL GLUTAMIDE; CITRUS AURANTIUM FRUIT OIL; BUTYLENE GLYCOL; ETHYLHEXYLGLYCERIN; CAMELLIA SINENSIS FLOWER; HIPPOPHAE RHAMNOIDES FRUIT; AMINOMETHYL PROPANEDIOL; CITRUS BIOFLAVONOIDS; .ALPHA.-TOCOPHEROL ACETATE; CARBOMER 940; POTASSIUM SORBATE; BRASSICA OLERACEA VAR. BOTRYTIS WHOLE; ASCORBYL PALMITATE

GLOSSIER INVISIBLE SHIELD DAILY SUNSCREEN BROAD SPECTRUM SPF 35

Active Ingredients

Avobenzone 3%

Homosalate 6%

Octisalate 5%

Purpose

Sunscreen

USES

- helps prevent sunburn
- if used as directed with other sun protection measures (see Directions), decreases the risk of skin cancer and early skin aging cause by the sun

Warnings

For extenal use only

Do not useon damaged or broken skin

WHEN USING

When using this productkeep out of eyes. Rinse with water to remove.

Stop use and ask a doctor ifrash occurs

Keep out of reach of children.If swallowed, get medical help or contact a Poison Control Center right away.

DIRECTIONS

- apply generously 15 minutes before sun exposure
- reapply at least every 2 hours
- use a water-resistant sunscreen if swimming or sweating
- Sun Protection Measures. Spending time in the sun

increases your risk of skin cancer and early skin aging. To decrease

this risk, regularly use a sunscreen with a Broad Spectrum SPF

value of 15 or higher and other sun protection measures including:

- limit time in the sun, especially from 10 a.m. - 2 p.m.
- wear long-sleeved shirts, pants, hats, and sunglasses
- children under 6 months of age: Ask a doctor

INACTIVE INGREDIENT

Inactive ingredients:Water, Butyloctyl Salicylate, Dipropylene Glycol, Methyl Trimethicone,
Biosaccharide Gum-4, Caprylyl Methicone, Propanediol, Bis-Ethylhexyl
Hydroxydimethoxy Benzylmalonate, Betaine, Acrylates Copolymer,
Ammonium Acryloyldimethyltaurate/VP Copolymer, Hydroxyacetophenone,
Phenoxyethanol, Hydrolyzed Wheat Protein/PVP Crosspolymer, Dibutyl
Lauroyl Glutamide, Dibutyl Ethylhexanoyl Glutamide, Citrus Aurantium
Dulcis (Orange) Peel Oil, Dipotassium Glycyrrhizate, Carbomer, Tocopheryl
Acetate, Aminomethyl Propanol, Butylene Glycol, Hippophae Rhamnoides
Fruit Extract, Disodium EDTA, Pentylene Glycol, Aloe Barbadensis Leaf
Extract, Silica, Bioflavonoids, Potassium Sorbate, Hydroxyphenyl
Propamidobenzoic Acid, Brassica Oleracea Italica (Broccoli) Extract,
Ethylhexylglycerin, Camellia Sinensis Leaf Extract, Ascorbyl Palmitate.

OTHER INFORMATION

- Protect the product in this container from excessive heat and direct sun

QUESTIONS or COMMENTS

visit www.glossier.com or call toll-free
1-844-OK-GTEAM 1-844-654-8326

PACKAGE LABEL

Primary Packaging

Secondary Package